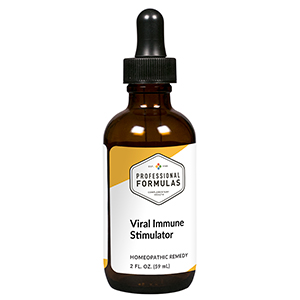 DRUG LABEL: Viral Immune Stimulator
NDC: 63083-6017 | Form: LIQUID
Manufacturer: Professional Complementary Health Formulas
Category: homeopathic | Type: HUMAN OTC DRUG LABEL
Date: 20190815

ACTIVE INGREDIENTS: SODIUM CHLORIDE 3 [hp_X]/59 mL; ASCLEPIAS TUBEROSA FLOWERING TOP 3 [hp_X]/59 mL; TRIFOLIUM PRATENSE FLOWER 3 [hp_X]/59 mL; ECHINACEA PURPUREA WHOLE 3 [hp_X]/59 mL; EUPHRASIA STRICTA 6 [hp_X]/59 mL; COW MILK 6 [hp_X]/59 mL; THUJA OCCIDENTALIS LEAF 6 [hp_X]/59 mL; FERROUS IODIDE 8 [hp_X]/59 mL; CAMPHOR (NATURAL) 12 [hp_X]/59 mL; CALCIUM ARSENATE 12 [hp_X]/59 mL; ICHTHAMMOL 12 [hp_X]/59 mL; VACCINIA VIRUS STRAIN NEW YORK CITY BOARD OF HEALTH LIVE ANTIGEN 30 [hp_X]/59 mL; MEASLES VIRUS 30 [hp_X]/59 mL; HUMAN HERPESVIRUS 1 30 [hp_X]/59 mL; INFLUENZA A VIRUS A/VICTORIA/2454/2019 IVR-207 (H1N1) ANTIGEN (FORMALDEHYDE INACTIVATED) 30 [hp_X]/59 mL; CYNANCHUM OTOPHYLLUM WHOLE 30 [hp_X]/59 mL; COXSACKIEVIRUS A21 30 [hp_X]/59 mL; JAPANESE ENCEPHALITIS VIRUS STRAIN NAKAYAMA-NIH ANTIGEN (FORMALDEHYDE INACTIVATED) 30 [hp_X]/59 mL; BACILLUS CALMETTE-GUERIN LIVE ANTIGEN, UNSPECIFIED SUBSTRAIN 30 [hp_X]/59 mL; HUMAN HERPESVIRUS 5 30 [hp_X]/59 mL
INACTIVE INGREDIENTS: ALCOHOL; WATER

X17

ACTIVE INGREDIENTS

Aqua marina 3X
Asclepias tuberosa 3X
Trifolium pratense 3X
Echinacea purpurea 3X
Euphrasia officinalis 6X
Lac vaccinum 6X
Thuja occidentalis 6X, 12X, 30X
Ferrum iodatum 8X
Camphora 12X
Calcarea arsenicica 12X
Ichthyolum 12X
Vaccinotoxinum 30X, 60X
Morbillinum 30X, 60X
Variolinum 30X, 60X
Influenzinum 30X, 60X
Vincetoxicum 30X, 60X
Coxsackievirus 30X, 60X
Encephalitis 30X, 60X
BCG 30X, 60X
Cytomegalovirus 30X, 60X

QUESTIONS

Professional Formulas

PO Box 2034 Lake Oswego, OR 97035

INDICATIONS

Temporarily relieves runny nose, chills, sweats, sore throat, minor aches and pains in the muscles or joints, or occasional headache.*

PURPOSE

*Claims based on traditional homeopathic practice, not accepted medical evidence. Not FDA evaluated.

WARNINGS

Persistent symptoms may be a sign of a serious condition. If symptoms persist or are accompanied by a fever, rash, or persistent headache, consult a doctor. Keep out of the reach of children. In case of overdose, get medical help or contact a poison control center right away. If pregnant or breastfeeding, ask a healthcare professional before use.

Keep out of the reach of children.

PREGNANCY OR BREAST FEEDING

If pregnant or breastfeeding, ask a healthcare professional before use.

DIRECTIONS

Place drops under tongue 30 minutes before/after meals. Adults and children 12 years and over: Take 10 drops up to 3 times per day. Consult a physician for use in children under 12 years of age.

OTHER INFORMATION

Tamper resistant. If seal is broken, do not use. After opening, close container tightly and store at room temperature away from heat.

INACTIVE INGREDIENTS

20% ethanol, purified water.

LABEL

Est 1985

Professional Formulas

Complementary Health

Viral Immune Stimulator

Homeopathic Remedy

2 FL. OZ. (59 mL)